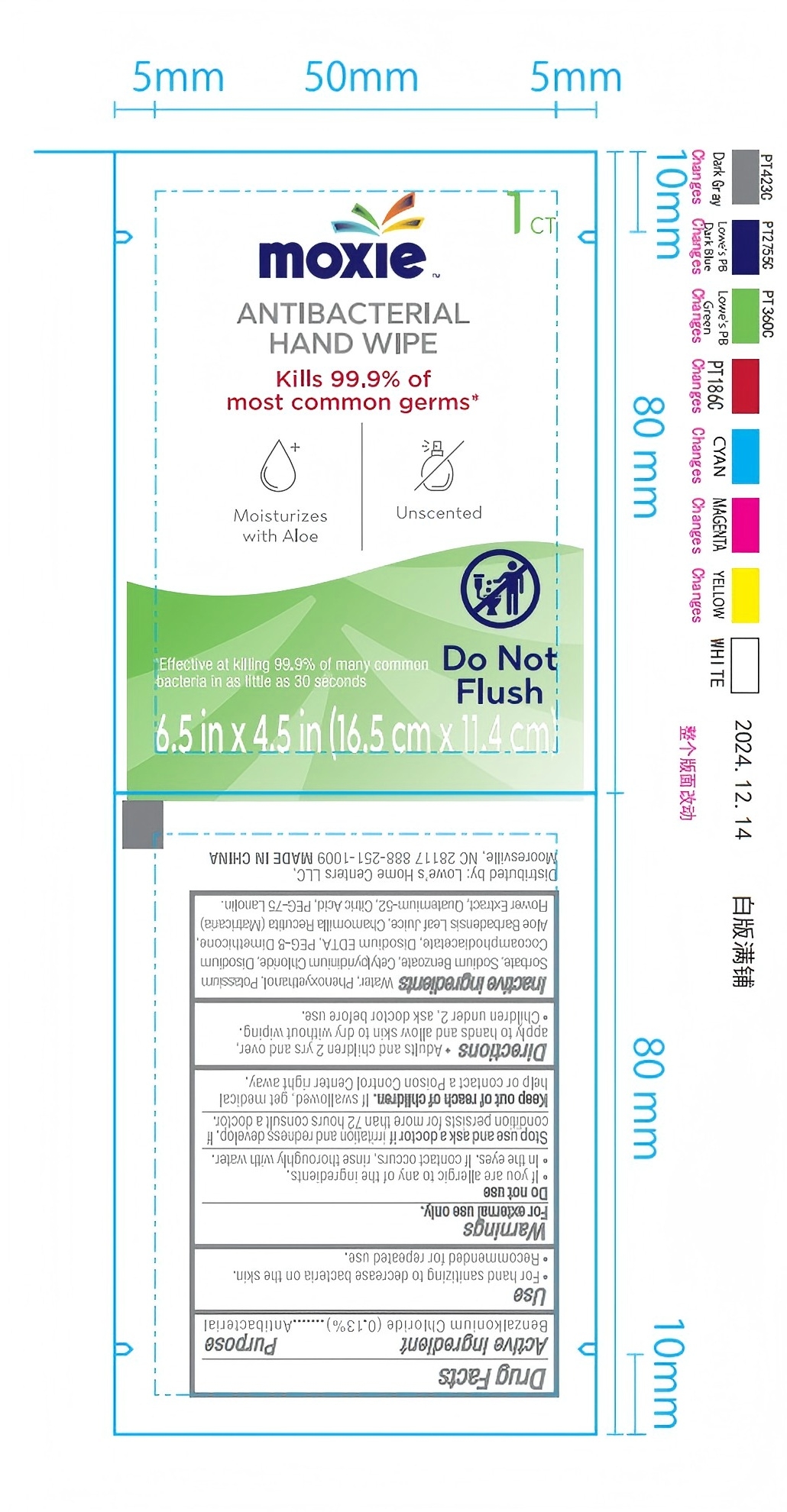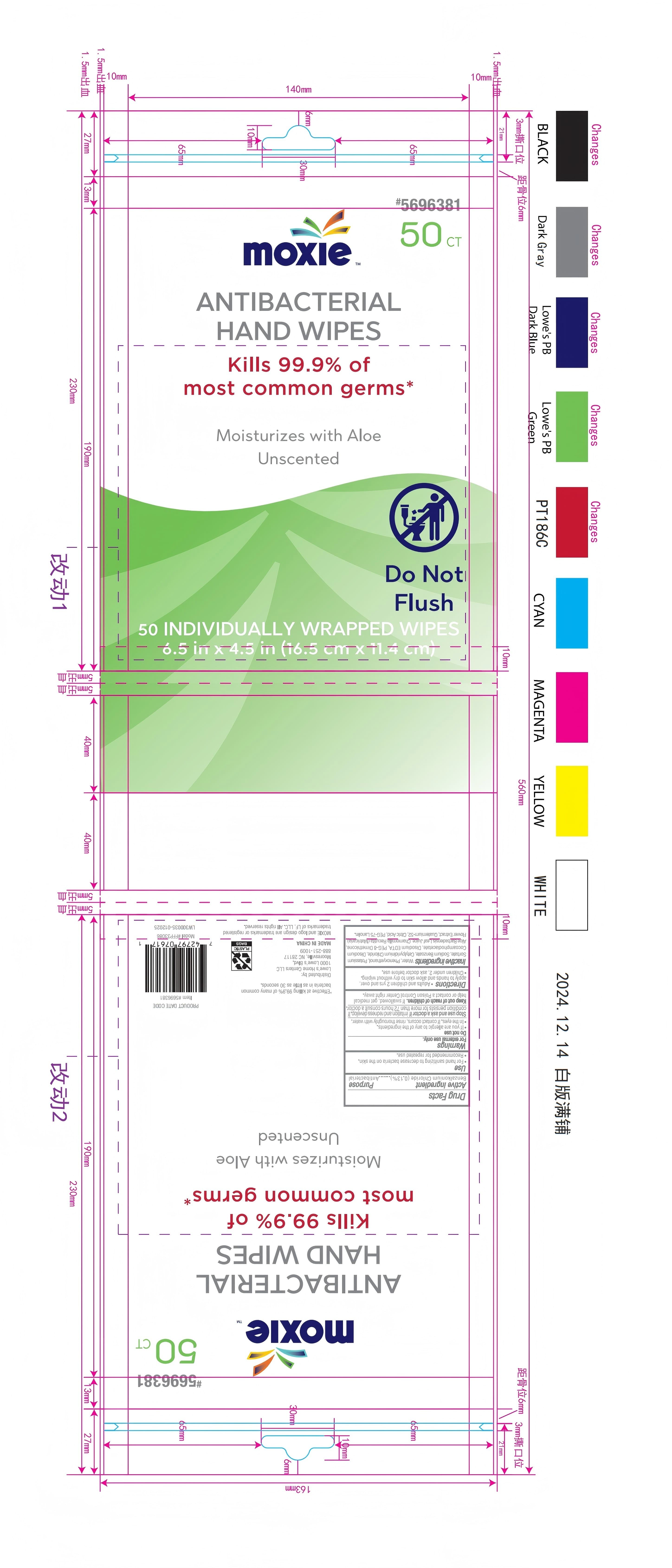 DRUG LABEL: Moxie Hand Wipes
NDC: 77720-035 | Form: CLOTH
Manufacturer: Skaffles Group
Category: otc | Type: HUMAN OTC DRUG LABEL
Date: 20250307

ACTIVE INGREDIENTS: BENZALKONIUM CHLORIDE 0.13 g/100 mL
INACTIVE INGREDIENTS: PEG-75 LANOLIN; POTASSIUM SORBATE; CETYLPYRIDINIUM CHLORIDE; QUATERNIUM-52; CITRIC ACID MONOHYDRATE; MATRICARIA CHAMOMILLA FLOWERING TOP OIL; PEG-8 DIMETHICONE; WATER; DISODIUM COCOAMPHODIACETATE; EDETATE DISODIUM; SODIUM BENZOATE; ALOE VERA LEAF

Moxie Antibacterial Hand Wipes

Active Ingredient

Benzalkonium Chloride (0.13%)

Purpose

Antibacterial

Use

- For hand sanitizing to decrease bacteria on the skin
- Recommended for repeated use.

Warnings

For external use only.

Do not use

- If you are allergic to any of the ingredients
- In the eyes. If contact occurs, rinse thoroughly with water.

Discontinue use if irritation and redness develop.If condition persists for more than 72 hours consult a doctor.

Directions

- Adults and children 2 yrs and over, apply to hands and allow skin to dry without wiping.
- Children under 2, ask doctor before use.

Inactive Ingredients

Water, Phenoxyethanol, Potassium Sorbate, Sodum Benzoate, Cetylpyridinium Chloride, Disodium Cocoamphodiacetate, Disodium EDTA, PEG-8 Dimethicone, Aloe Barbadensis Leaf Juice, Chamomilla Recutita (Matricacria), Flower Extract, Quaternium-52, Citric Acid, PEG075 Lanolin.

Principal Display Panel

Moxie

ANTIBACTERIAL HAND WIPES

Kills 99.9% of most comon gems

Moisturizes with Aloe

Unscented

Do Not Flush

*Effective at killing 99.9% of many common bacteria in as little as 30 seconds

6.5 in x 4.5 in (16.5 cm x 11.4 cm)

1CT

Distributed by: Lowe's Home Centers LLC,

Mooresville NC 28117 888-251-009

MADE IN CHINA

Moxie

ANTIBACTERIAL HAND WIPES

Kills 99.9% of most comon gems

Moisturizes with Aloe

Unscented

Do Not Flush

50 INDIVIDUALLY WRAPPED WIPES

6.5 in x 4.5 in (16.5 cm x 11.4 cm)

50CT

*Effective at killing 99.9% of many common bacteria in as little as 30 seconds

Distributed by: Lowe's Home Centers LLC,

Mooresville NC 28117 888-251-009

MADE IN CHINA

Moxie and logo design are trademarks or registered trademarks of LF, LLC. All rights reserved.

PRODUCT DATE CODE